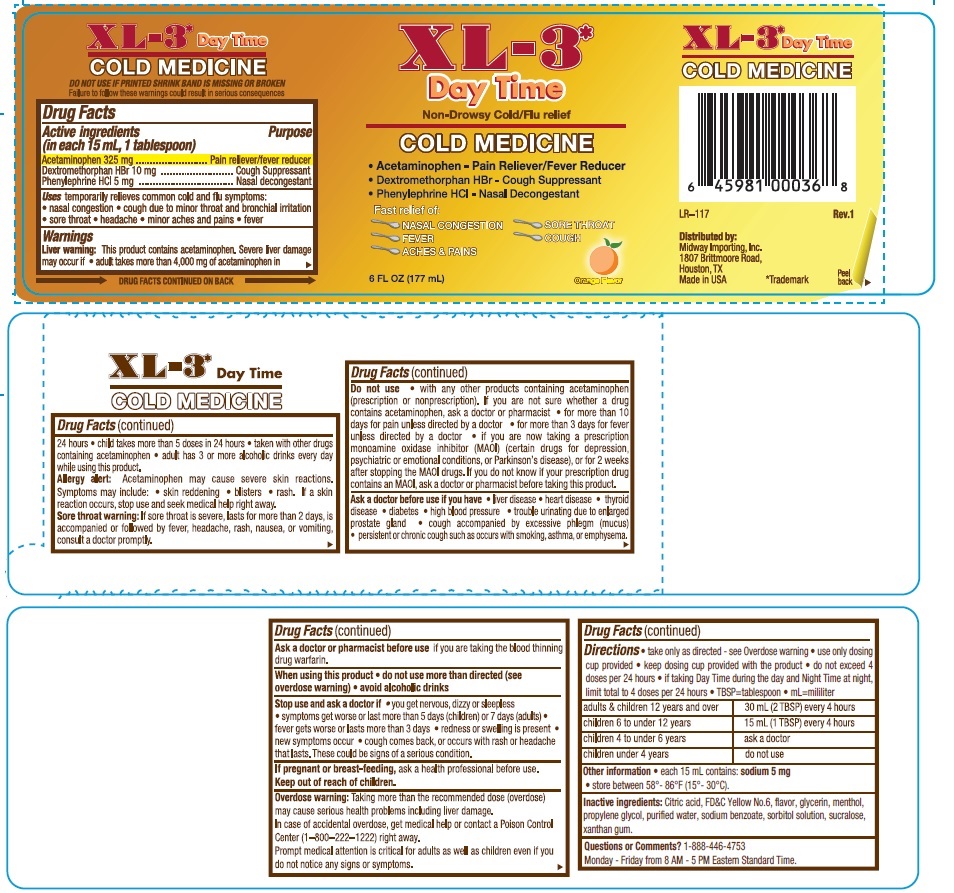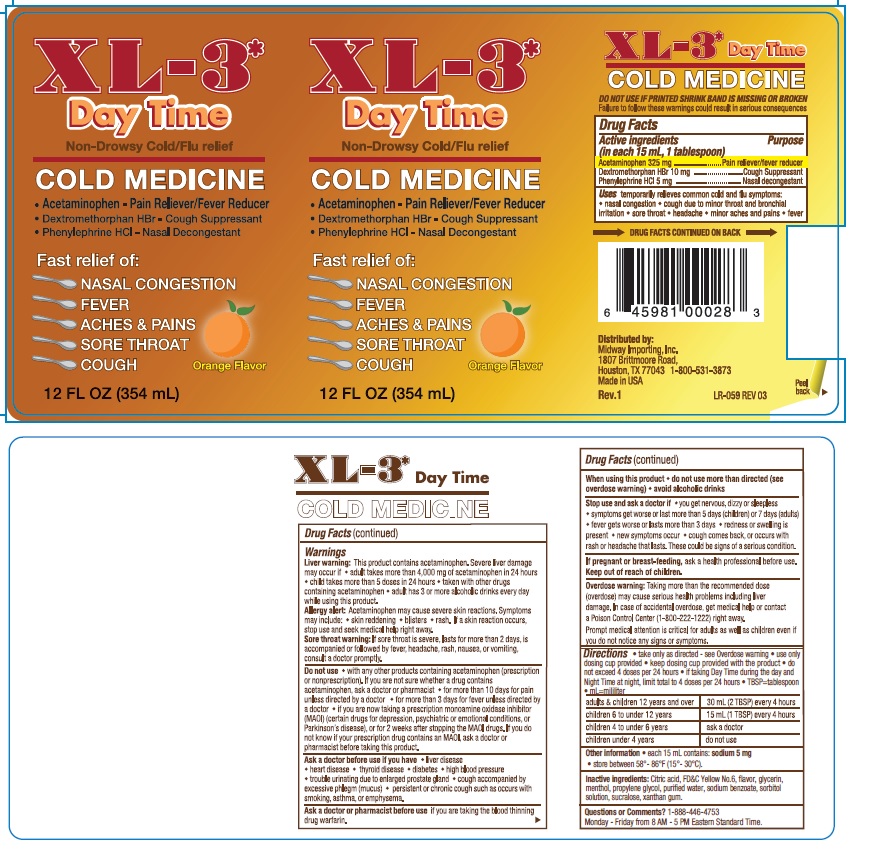 DRUG LABEL: XL-3 Day Time
NDC: 84379-441 | Form: LIQUID
Manufacturer: Rnv LLC
Category: otc | Type: HUMAN OTC DRUG LABEL
Date: 20260127

ACTIVE INGREDIENTS: DEXTROMETHORPHAN HYDROBROMIDE 10 mg/15 mL; ACETAMINOPHEN 325 mg/15 mL; PHENYLEPHRINE HYDROCHLORIDE 5 mg/15 mL
INACTIVE INGREDIENTS: CITRIC ACID; PROPYLENE GLYCOL; FD&C YELLOW NO. 6; MENTHOL; GLYCERIN; WATER; XANTHAN GUM; SODIUM BENZOATE; SORBITOL SOLUTION; SUCRALOSE

XL-3 Day Time

ACTIVE INGREDIENT

Acetaminophen 325 mg

Dextromethorphan HBr 10 mg

Phenylephrine HCl 5 mg

PURPOSE

Pain reliever/fever reducer

Cough Suppressant

Nasal Decongestant

INDICATIONS AND USAGE

Uses temporarily relieves common cold and flu symptoms:

• nasal congestion • cough due to minor throat and bronchial irritation

• sore throat • headache • minor aches and pains • fever

Warnings

Liver warning: This product contains acetaminophen. Sever liver damage may occur if

- adult takes more than 5 doses in 24 hours
- taken with other drugs containing acetaminophen
- adults has 3 or more alcoholic drinks every day while using this product

Allergy alert: Acetaminophen may cause sever skin reactions. Symptoms may include:

• skin reddening

• blisters

• ras.

If skin reaction occurs, stop use and seek medical help right away.

Sore throat warning: If sore throat is sever, lasts for more than 2 days, is accompanied or followed by fever, headache, rash, nausea, or vomiting, consult a doctor promptly.

Do not use

• with any other products containing acetaminophen (prescription or nonprescription). If you are not sure whether a drug contains acetaminophen, ask a doctor or pharmacist
• for more than 10 days for pain unless directed by a doctor
• for more than 3 days or fever unless directed by a doctor
• if you are now taking a prescription monoamine oxidase inhibitor (MAOI) (certain drugs for depression, psychiatric or emotional conditions, or Parkinson's diseas), or for 2 weeks after stopping the MAOI drugs. If you do not know if your prescription drug contains an MAOI, ask a doctor or pharmacist before taking this product.

Ask a doctor before use if you have

• liver disease
• heart disease
• thyroid disease
• diabete
• high blood pressure
• trouble urinating due to enlarged prostate gland
• cough accompanied by excessive phlegm (mucus)
• persistent or chronic cough such as occurs with smoking, asthma, or emphysema.

Ask a doctor or pharmacist before use if you are taking the blood thinning drug warfarin.

When using this product

- do not use more than directed (see overdose warning)
- avoid alcoholic drinks

Stop use and ask a doctor if

- you get nervous, dizzy or sleepless
- symptoms get worse or last more than 5 days (children) or 7 days (adults)
- fever gets worse or lasts more than 3 days
- redness or swelling is present
- new symptoms occur
- cough comes back, or occurs with rash or headache that lasts. These could be signs of a serious condition.

PREGNANCY OR BREAST FEEDING

If pregnant or breast-feeding, ask a health professional before use.

Keep out of reach of children.

OVERDOSAGE

Overdose warning: Taking more than the recommended dose (overdose) may cause serious health problems including liver damamge. In case of accidental overdose, get medical help or contact a Poison Control Center (1-800-222-1222) right away.

Prompt medical attention is critical for adults as well as children even if you do not notice any signs or symptoms.

Directions

- take only as directed- see Overdose warning
- use only dosing cup provided
- keep dosing cup provided with the product
- do not exceed 4 doses per 24 hours
- if taking Day Time during the day and Night Time at night, limit the total to 4 doses per 24 hours
- TBSP=tablespoon
- mL=mililiter

adults & children 12 years and over | 30 mL (2 TBSP) every 4 hours
children 6 to under 12 years | 15 mL (1 TBSPO) every 4 hours
children 4 to under 6 years | ask a doctor
children under 4 years | do not use

Other information

- each 15 mL contains: sodium 5 mg
- store between 58º - 86ºF (15º-30ºC).

INACTIVE INGREDIENT

Inactive ingredients: Citric acid, FD&C Yellow No 6, flavor, glycerin, menthol, propylene glycol, purified water, sodium benzoate, sorbitol solution, sucralose, xanthan gum

Questions or Comments? 1-888-446-4753

Monday - Friday from 8 AM - 5 PM Eastern Standard Time